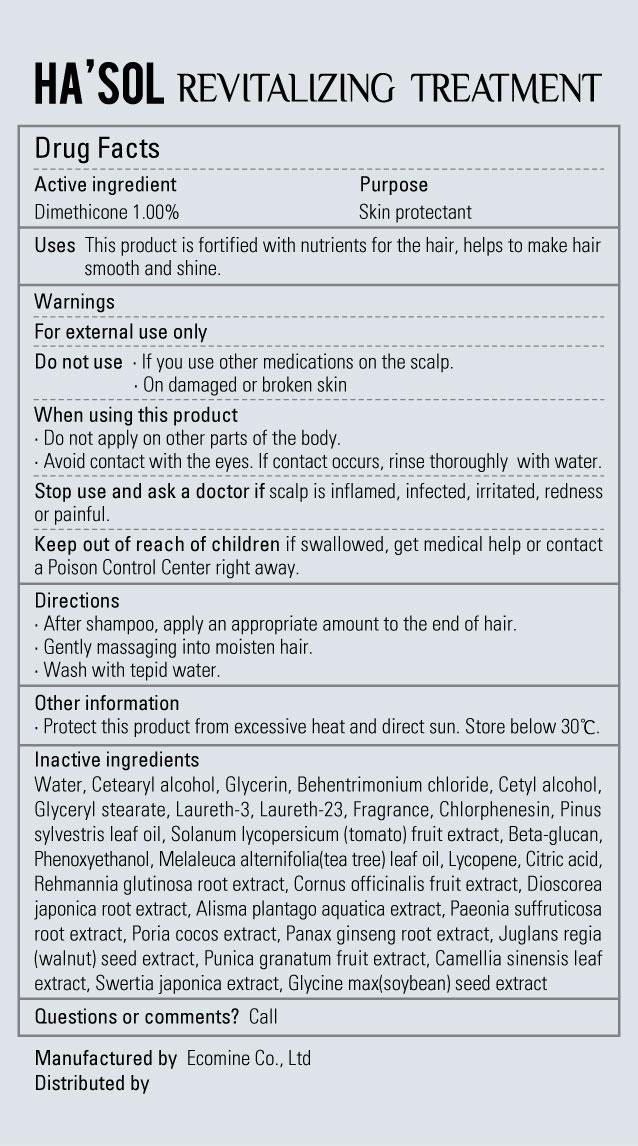 DRUG LABEL: Hasol Revitalizing Treatment
NDC: 51270-115 | Form: GEL
Manufacturer: Ecomine Co Ltd
Category: otc | Type: HUMAN OTC DRUG LABEL
Date: 20130701

ACTIVE INGREDIENTS: DIMETHICONE 1.0 g/300 g
INACTIVE INGREDIENTS: WATER; CETOSTEARYL ALCOHOL; GLYCERIN; BEHENTRIMONIUM CHLORIDE; CETYL ALCOHOL; GLYCERYL MONOSTEARATE; LAURETH-3; LAURETH-23; CHLORPHENESIN; PINE NEEDLE OIL (PINUS SYLVESTRIS); TOMATO; PHENOXYETHANOL; TEA TREE OIL; LYCOPENE; CITRIC ACID MONOHYDRATE; REHMANNIA GLUTINOSA ROOT; CORNUS OFFICINALIS FRUIT; DIOSCOREA JAPONICA TUBER; ALISMA PLANTAGO-AQUATICA TOP; PAEONIA SUFFRUTICOSA ROOT; FU LING; ASIAN GINSENG; ENGLISH WALNUT; POMEGRANATE; GREEN TEA LEAF; SWERTIA JAPONICA; SOYBEAN

Hasol Revitalizing Treatment

Drug Facts

Active ingredient

Dimethicone 1.00%

Purpose

Skin protectant

Keep out of Reach of children

Stop use and ask a doctor if scalp is inflamed, infected, irritated, redness or painful.

Keep out of reach of children if swallowed, get medical help or contact a Poison Control Center right away.

Indication & Usage

Directions
■ After shampoo, apply an appropriate amount to the end of hair.
■ Gently massaging into moisten hair.
■ Wash with tepid water.

Warnings

For external use only

Do not use ■ If you use other medications on the scalp.
■ On damaged or broken skin

When using this product
■ Do not apply on other parts of the body
■ Avoid contact with the eyes. If contact occurs, rinse thoroughly with water.

Dosage & Administration

Uses ■ This product is fortified with nutrients for the hair, helps to make hair smooth and shine.

Inactive ingredient

Water, Cetearyl alcohol, Glycerin, Behentrimonium chloride, Cetyl alcohol, Glyceryl stearate, Laureth-3, Laureth-23, Fragrance, Chlorphenesin, Pinus sylvestris leaf oil, Solanum lycopersicum (tomato) fruit extract, Beta-glucan, Phenoxyethanol, Melaleuca alternifolia(tea tree) leaf oil, Lycopene, Citric acid, Rehmannia glutinosa root extract, Cornus officinalis fruit extract, Dioscorea japonica root extract, Alisma plantago aquatica extract, Paeonia suffruticosa root extract, Poria cocos extract, Panax ginseng root extract, Juglans regia(walnut) seed extract, Punica granatum fruit extract, Camellia sinensis leaf extract, Swertia japonica extract, Glycine max(soybean) seed extract

Hasol Revitalizing Treatment

Net WT. 10.14 FL OZ(300ml)